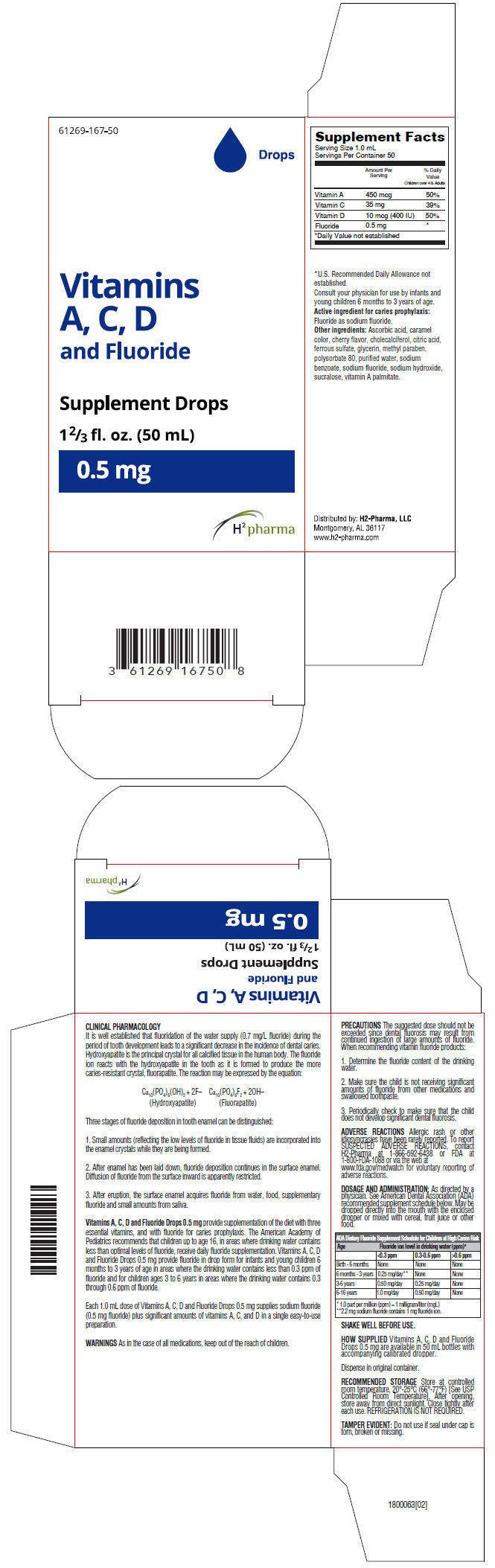 DRUG LABEL: Vitamins A, C, D and Fluoride Drops
NDC: 61269-167 | Form: SOLUTION/ DROPS
Manufacturer: H2-Pharma, LLC
Category: other | Type: DIETARY SUPPLEMENT
Date: 20250916

ACTIVE INGREDIENTS: VITAMIN A PALMITATE 450 [iU]/1 mL; ASCORBIC ACID 35 mg/1 mL; CHOLECALCIFEROL 10 [iU]/1 mL; SODIUM FLUORIDE 0.5 mg/1 mL
INACTIVE INGREDIENTS: CARAMEL; CITRIC ACID MONOHYDRATE; FERROUS SULFATE; CHERRY; GLYCERIN; METHYLPARABEN; POLYSORBATE 80; WATER; SODIUM BENZOATE; SODIUM HYDROXIDE; SUCRALOSE

Vitamins A, C, D and Fluoride Drops

STATEMENT OF IDENTITY

Supplement Facts
Serving Size 1.0 mL
Servings Per Container 50
 | Amount Per Serving | % Daily Value
Children over 4 & Adults
Vitamin A | 450 mcg | 50%
Vitamin C | 35 mg | 39%
Vitamin D | 10 mcg (400 IU) | 50%
Fluoride | 0.5 mg | [Daily Value not established]

*U.S. Recommended Daily Allowance not established.

Consult your physician for use by infants and young children 6 months to 3 years of age.

Active ingredient for caries prophylaxis: Fluoride as sodium fluoride.

Other ingredients: Ascorbic acid, caramel color, cherry flavor, cholecalciferol, citric acid, ferrous sulfate, glycerin, methyl paraben, polysorbate 80, purified water, sodium benzoate, sodium fluoride, sodium hydroxide, sucralose, vitamin A palmitate.

CLINICAL PHARMACOLOGY

It is well established that fluoridation of the water supply (0.7 mg/L fluoride) during the period of tooth development leads to a significant decrease in the incidence of dental caries. Hydroxyapatite is the principal crystal for all calcified tissue in the human body. The fluoride ion reacts with the hydroxyapatite in the tooth as it is formed to produce the more caries-resistant crystal, fluorapatite. The reaction may be expressed by the equation:

Ca10(PO4)6(OH)2 + 2F− Ca10(PO4)6F2 + 2OH−

(Hydroxyapatite)

(Fluorapatite)

Three stages of fluoride deposition in tooth enamel can be distinguished:

1. Small amounts (reflecting the low levels of fluoride in tissue fluids) are incorporated into the enamel crystals while they are being formed.
2. After enamel has been laid down, fluoride deposition continues in the surface enamel. Diffusion of fluoride from the surface inward is apparently restricted.
3. After eruption, the surface enamel acquires fluoride from water, food, supplementary fluoride and small amounts from saliva.

Vitamins A, C, D and Fluoride Drops 0.5 mg provide supplementation of the diet with three essential vitamins, and with fluoride for caries prophylaxis. The American Academy of Pediatrics recommends that children up to age 16, in areas where drinking water contains less than optimal levels of fluoride, receive daily fluoride supplementation. Vitamins A, C, D and Fluoride Drops 0.5 mg provide fluoride in drop form for infants and young children 6 months to 3 years of age in areas where the drinking water contains less than 0.3 ppm of fluoride and for children ages 3 to 6 years in areas where the drinking water contains 0.3 through 0.6 ppm of fluoride.

Each 1.0 mL dose of Vitamins A, C, D and Fluoride Drops 0.5 mg supplies sodium fluoride (0.5 mg fluoride) plus significant amounts of vitamins A, C, and D in a single easy-to-use preparation.

WARNINGS

As in the case of all medications, keep out of the reach of children.

PRECAUTIONS

The suggested dose should not be exceeded since dental fluorosis may result from continued ingestion of large amounts of fluoride. When recommending vitamin fluoride products:

1. Determine the fluoride content of the drinking water.
2. Make sure the child is not receiving significant amounts of fluoride from other medications and swallowed toothpaste.
3. Periodically check to make sure that the child does not develop significant dental fluorosis.

ADVERSE REACTIONS

Allergic rash or other idiosyncrasies have been rarely reported. To report SUSPECTED ADVERSE REACTIONS, contact H2-Pharma at 1-866-592-6438 or FDA at 1-800-FDA-1088 or via the web at www.fda.gov/medwatch for voluntary reporting of adverse reactions.

DOSAGE AND ADMINISTRATION

As directed by a physician. See American Dental Association (ADA) recommended supplement schedule below. May be dropped directly into the mouth with the enclosed dropper or mixed with cereal, fruit juice or other food.

ADA Dietary Fluoride Supplement Schedule for Children at High Caries Risk
Age | Fluoride ion level in drinking water (ppm) [1.0 part per million (ppm) = 1 milligram/liter (mgL)]
 | <0.3 ppm | 0.3-0.6 ppm | >0.6 ppm
Birth - 6 months | None | None | None
6 months - 3 years | 0.25 mg/day [2.2 mg sodium fluoride contains 1 mg fluoride ion.] | None | None
3-6 years | 0.50 mg/day | 0.25 mg/day | None
6-16 years | 1.0 mg/day | 0.50 mg/day | None

SHAKE WELL BEFORE USE.

HOW SUPPLIED

Vitamins A, C, D and Fluoride Drops 0.5 mg are available in 50 mL bottles with accompanying calibrated dropper.

Dispense in original container.

RECOMMENDED STORAGE

Store at controlled room temperature, 20°-25°C (66°-77°F) [See USP Controlled Room Temperature]. After opening, store away from direct sunlight. Close tightly after each use. REFRIGERATION IS NOT REQUIRED.

TAMPER EVIDENT: Do not use if seal under cap is torn, broken or missing.

HEALTH CLAIM

Distributed by: H2-Pharma, LLC
Montgomery, AL 36117

PRINCIPAL DISPLAY PANEL - 50 mL Bottle Carton

61269-167-50

Drops

Vitamins
A, C, D
and Fluoride

Supplement Drops

1⅔ fl. oz. (50 mL)

0.5 mg

H^2 pharma